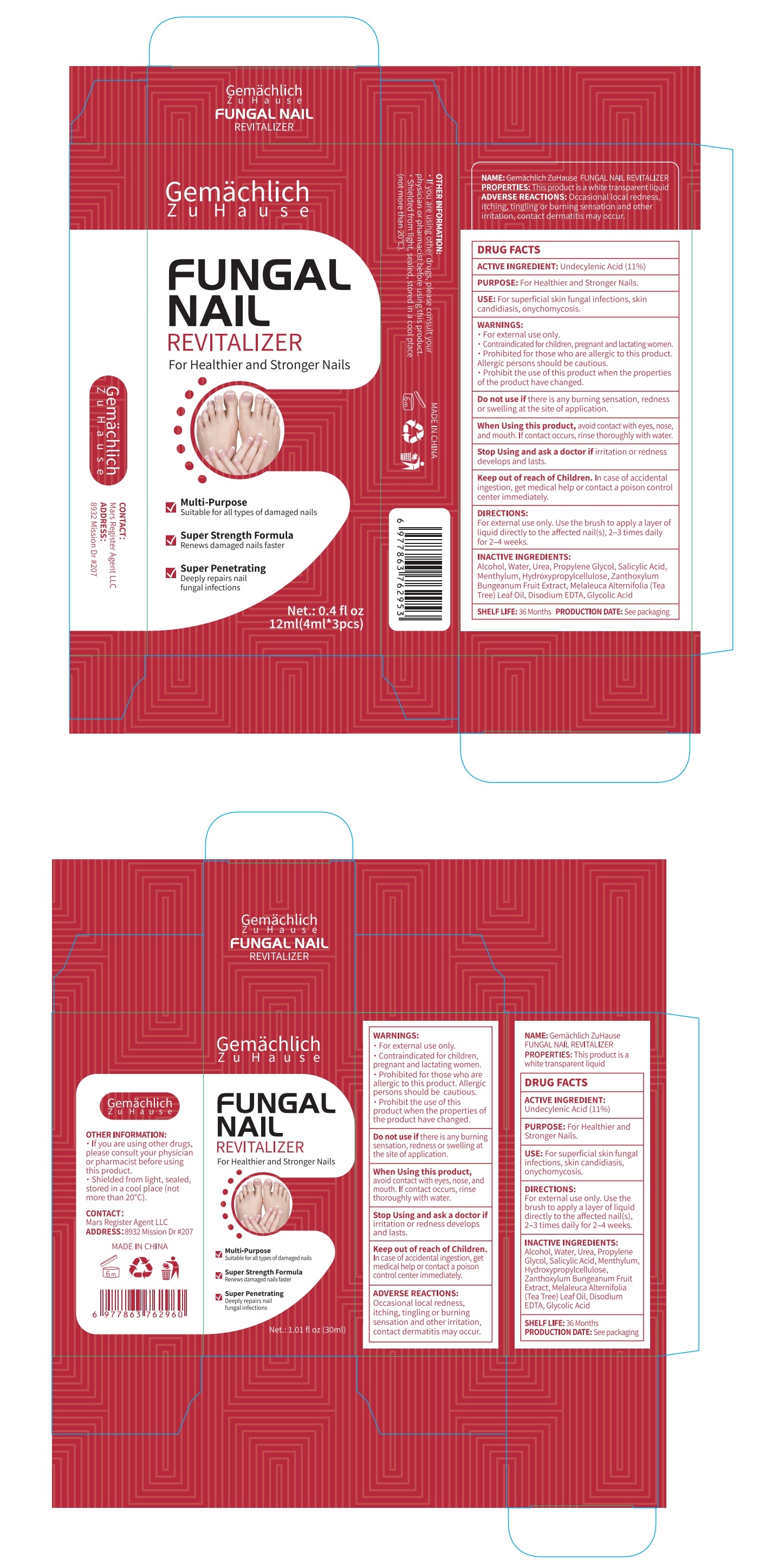 DRUG LABEL: Gemachlich ZuHause Fungal Nail Revitalizer
NDC: 76986-007 | Form: LIQUID
Manufacturer: Guangdong Quadrant Ecological Technology Co., Ltd.
Category: otc | Type: HUMAN OTC DRUG LABEL
Date: 20250610

ACTIVE INGREDIENTS: UNDECYLENIC ACID 11 g/100 mL
INACTIVE INGREDIENTS: ALCOHOL; HYDROXYPROPYLCELLULOSE; ZANTHOXYLUM BUNGEANUM FRUIT; GLYCOLIC ACID; PROPYLENE GLYCOL; SALICYLIC ACID; EDETATE DISODIUM; WATER; UREA; MENTHOL; MELALEUCA ALTERNIFOLIA (TEA TREE) LEAF OIL

76986-007

Active Ingredient

Undecylenic Acid 11%

Purpose

For Healthier and Stronger Nails.

Use

For superficial skin fungal infections, skin candidiasis, onychomycosis.

Warnings

.For external use only.
.Contraindicated for children, pregnant and lactating women.
.Prohibited for those who are allergic to this product. Allergic persons should be cautious.
.Prohibit the use of this product when the properties of the product have changed.

Do not use if there is any burning sensation, redness or swelling at the site of application.

When Using

When Using this product, avoid contact with eyes, nose, and mouth. If contact occurs, rinse thoroughly with water.

Stop Use

Stop Using and ask a doctor if irritation or redness develops and lasts.

Ask Doctor

In case of accidental ingestion, get medical help or contact a poison control center immediately.

Keep Out Of Reach Of Children

Directions

For external use only. Use the brush to apply a layer ofliquid directly to the affected nail(s),2-3 times dailyfor 2-4 weeks.

Other information

· If you are using other drugs, please consult your physician or pharmacist before using this product.
· Shielded from light, sealed, stored in a cool place (not more than 20°C).

Inactive ingredients

Alcohol, Water, Urea, Propylene Glycol, Salicylic Acid, Menthylum, Hydroxypropylcellulose, Zanthoxylum Bungeanum Fruit
Extract, Melaleuca Alternifolia (Tea Tree) Leaf Oil, Disodium EDTA, Glycolic Acid